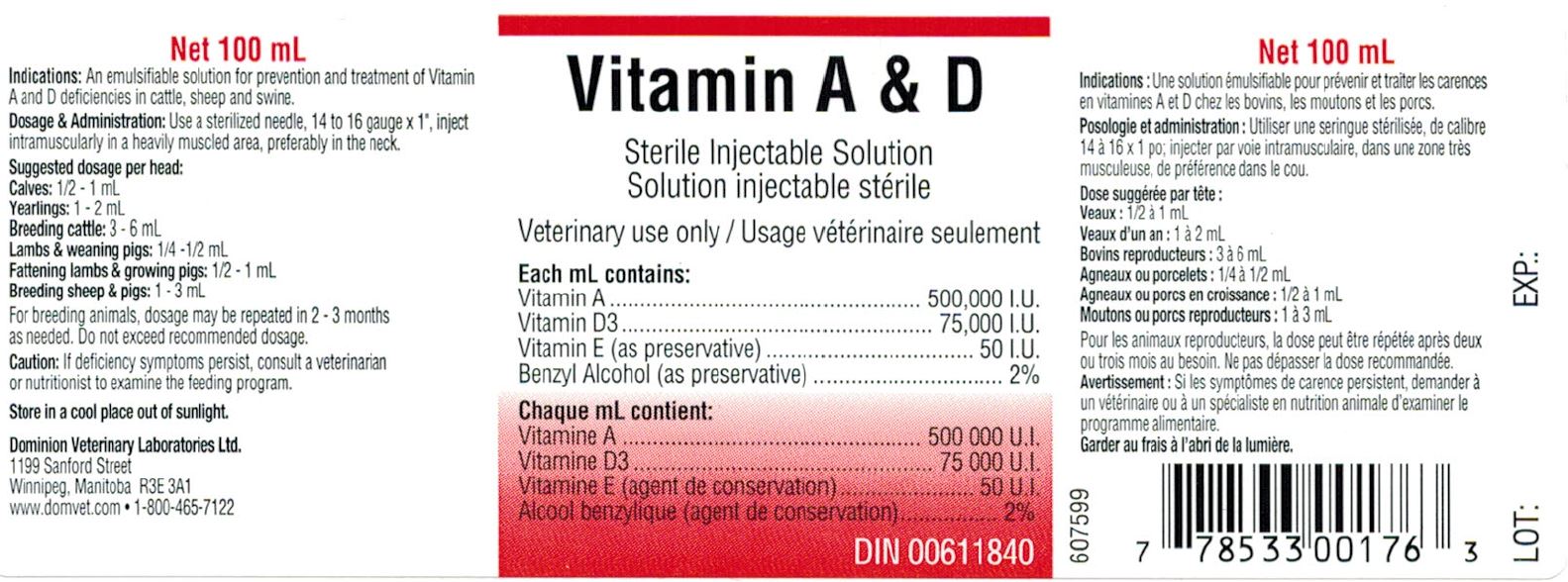 DRUG LABEL: VITAMIN A AND D
NDC: 64120-109 | Form: INJECTION, SOLUTION
Manufacturer: DOMINION VETERINARY LABORATORIES LTD.
Category: animal | Type: OTC ANIMAL DRUG LABEL
Date: 20211110

ACTIVE INGREDIENTS: VITAMIN A 500000 [iU]/1 mL; CHOLECALCIFEROL 75000 [iU]/1 mL
INACTIVE INGREDIENTS: .ALPHA.-TOCOPHEROL; BENZYL ALCOHOL

DOMINION VETERINARY LABORATORIES - VITAMIN A & D STERILE INJECTABLE SOLUTION

INDICATIONS:

AN EMULSIFIABLE SOLUTION FOR PREVENTION AND TREATMENT OF VITAMIN A AND D DEFICIENCIES IN CATTLE, SHEEP AND SWINE.